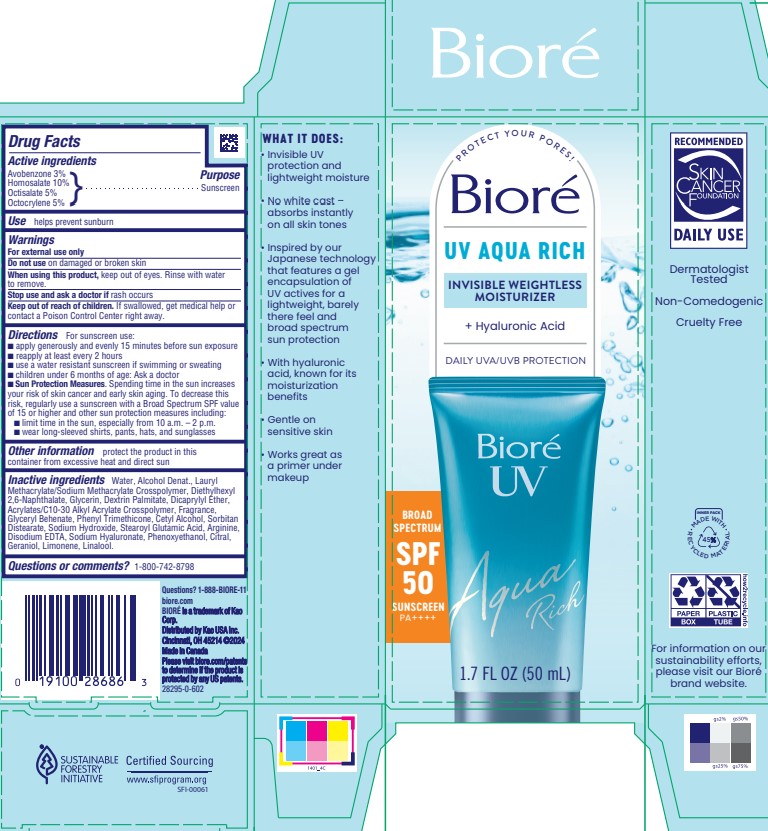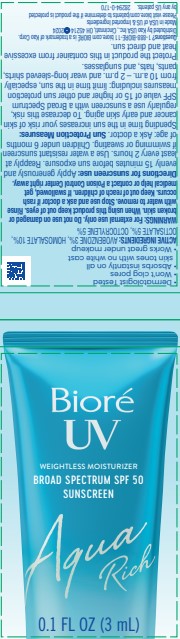 DRUG LABEL: Biore Aqua Rich UV
NDC: 10596-195 | Form: LIQUID
Manufacturer: KAO USA
Category: otc | Type: HUMAN OTC DRUG LABEL
Date: 20250212

ACTIVE INGREDIENTS: OCTOCRYLENE 5 g/100 mL; OCTISALATE 5 g/100 mL; HOMOSALATE 10 g/100 mL; AVOBENZONE 3 g/100 mL
INACTIVE INGREDIENTS: GLYCERYL MONOBEHENATE; LAURYL METHACRYLATE; LINALOOL, (+/-)-; ARGININE; SORBITAN DISTEARATE; CITRAL; GERANIOL; LIMONENE, (+)-; PHENOXYETHANOL; DICAPRYLYL ETHER; PHENYL TRIMETHICONE; SODIUM HYDROXIDE; DIETHYLHEXYL 2,6-NAPHTHALATE; GLYCERIN; DEXTRIN PALMITATE (CORN; 20000 MW); CETYL ALCOHOL; WATER; ALCOHOL; STEAROYL GLUTAMIC ACID; EDETATE DISODIUM ANHYDROUS; HYALURONATE SODIUM

Biore Aqua Rich UV SPF 50

Active ingredients

Avobenzone 3%

Homosalate 10%

Octisalate 5%

Octocrylene 5%

Purpose

Sunscreen

Use

helps prevent sunburn

Warnings

For external use only

Do not use on damaged or broken skin

When using this product, keep out of eyes. Rinse with water to remove.

Stop use and ask a doctor if rash occurs

Keep out of reach of children. If swallowed, get medical help or contact a Poison Control Center right away.

Directions

For sunscreen use:

- apply generously and evenly 15 minutes before sun exposure
- reapply at least every 2 hours
- use a water resistant sunscreen if swimming or sweating
- children under 6 months of age: Ak a doctor
- Sun Protection Measures. Spending time in the sun increases your risk of skin cancer and early skin aging. To decrease this risk, regularly use a sunscreen with a Broad Spectrum SPF value of 15 or higher and other sun protection measures including:

•limit time in the sun, especially from 10 a.m. - 2 p.m.

•wear long-sleeved shirts, pants, hat, and sunglasses

Other information

protect the product in this container from excessive heat and direct sun

Inactive ingredients

Water, alcohol denat., lauryl methacrylate/sodium methacrylate crosspolymer, diethylhexyl 2,6-naphthalate, glycerin, dextrin palmitate, dicaprylyl ether, acrylates/C10-30 alkyl acrylate crosspolymer, fragrance, glyceryl behenate, phenyl trimethicone, cetyl alcohol, sorbitan distearate, sodium hydroxide, stearoyl glutamic acid, arginine, disodium EDTA, sodium haluronate, phenoxyethanol, citral, geraniol, limonene, linalool.

Questions

or comments? 1-800-BIORE-11

Questions? 1-888-BIORE-11

biore.com

BIORE is a trademark of Kao Corp.

Distributed by Kao USA Inc.,

Cincinnatti, OH 45214 ©2024

Made in Canada

PACKAGE LABEL

Biore

UV Aqua Rich

Invisible Weightless Moisturizer

+Hyaluronic acid

DAILY UVA/UVB PROTECTION

BROAD SPECTRUM SPF 50 SUNSCREEN